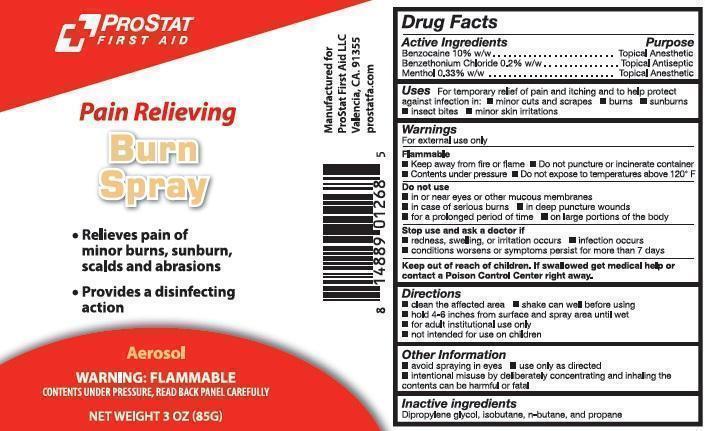 DRUG LABEL: ProStat Burn First Aid
NDC: 58228-0105 | Form: AEROSOL, SPRAY
Manufacturer: ProStat First Aid
Category: otc | Type: HUMAN OTC DRUG LABEL
Date: 20140307

ACTIVE INGREDIENTS: BENZETHONIUM CHLORIDE 170 mg/85 g; BENZOCAINE 8500 mg/85 g; MENTHOL 281 mg/85 g
INACTIVE INGREDIENTS: DIPROPYLENE GLYCOL; ISOBUTANE; BUTANE; PROPANE

ProStat Pain Relieving Burn Spray

Active Ingredients

Benzocaine 10% w/w
Benzethonium Chloride .2% w/w
Menthol .33% w/w

Purpose

Topical Anesthetic
Topical Antiseptic
Topical Anesthetic

Uses

For temporary relief of pain, itching and to help protect against infection in

minor cuts and scrapes
burns
sunburns
insect bites
minor skin irritations

Warnings

For external use only

Flammable
keep away from fire or flame
contents under pressure
do not puncture or incinerate container
do not expose to temperatures above 120° F

Do not use

in or near eyes or other mucous membranes
in case of serious burns
in deep puncture wounds
for prolonged period of time
on large portions of the body

Stop use and ask a doctor if

redness, swelling, or irritation occurs
infection occurs
conditions worsen or symptoms persist for more than 7 days

Directions

clean the affected area
shake can well before using
hold 4-6 inches from surface and spray area until wet
for adult institutional use only
not intended for use on children

Other information

avoid spraying in eyes
use only as directed
intentional misuse by deliberately concentrating and inhaling the contents may be harmful or fatal

Inactive Ingredients

dipropylene glycol, isobutane, n-butane, propane